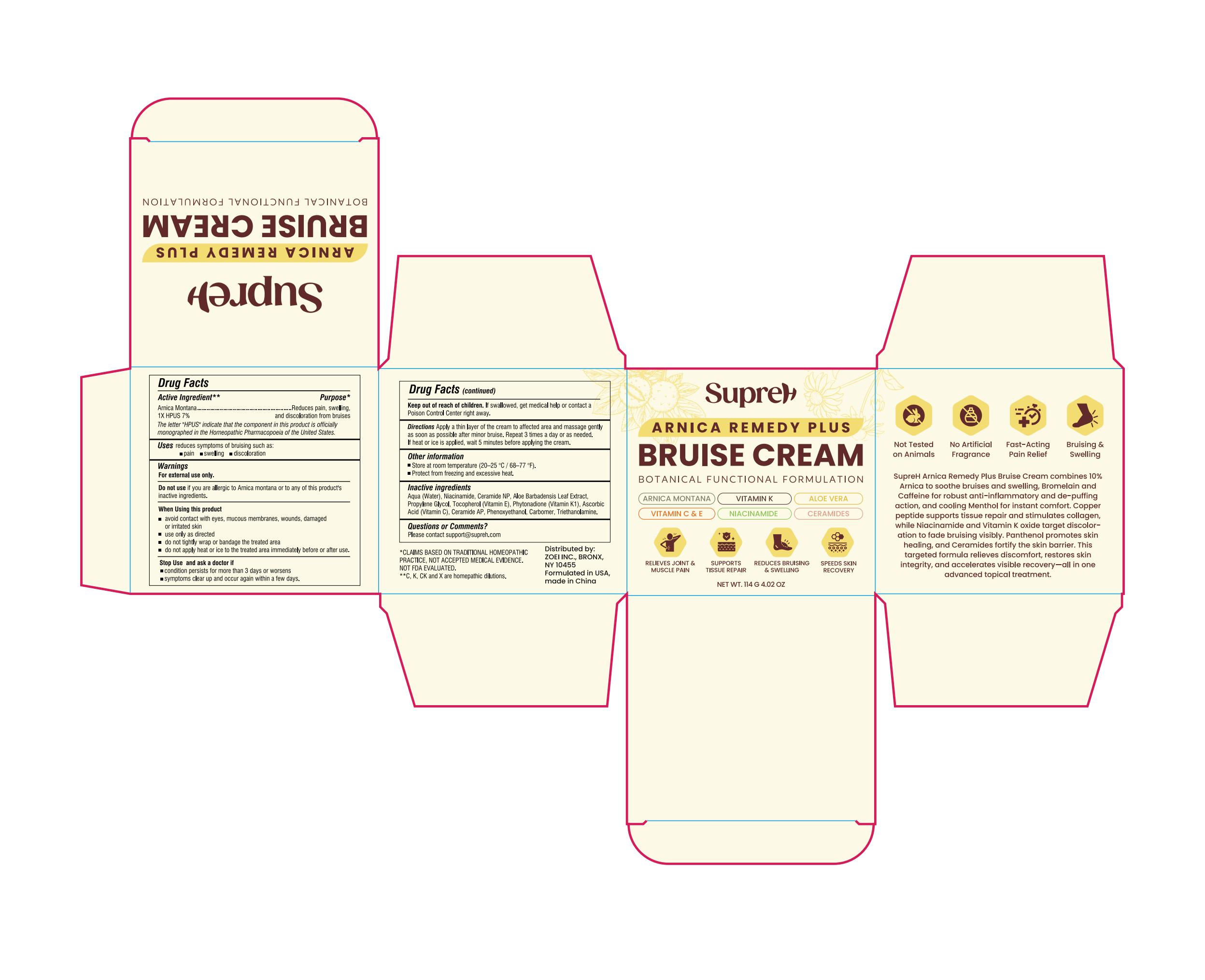 DRUG LABEL: SupreH Arnica Bruise Cream
NDC: 83818-025 | Form: CREAM
Manufacturer: Shenzhen Xinxin Yunhai Technology Co., Ltd.
Category: otc | Type: HUMAN OTC DRUG LABEL
Date: 20250907

ACTIVE INGREDIENTS: ARNICA MONTANA 7 g/100 g
INACTIVE INGREDIENTS: CARBOMER; CERAMIDE AP; NIACINAMIDE; ALOE BARBADENSIS LEAF; ALPHA-TOCOPHEROL; ASCORBIC ACID; PHYTONADIONE; TRIETHANOLAMINE; PHENOXYETHANOL; CERAMIDE NP; PROPYLENE GLYCOL

83818-025

Active Ingredient

Arnica Montana 1X HPUS 7%

Purpose

Reduces pain, swelling, and discoloration from bruises

Use

reduces symptoms of bruising such as: 1. pain 2. swelling 3. discoloration

Warnings

For external use only

Do not use

if you are allergic to Arnica montana or to any of this product's inactive ingredients.

When Using this product

• avoid contact with eyes, mucous membranes, wounds, damaged or irritated skin
• use only as directed
• do not tightly wrap or bandage the treated area
• do not apply heat or ice to the treated area immediately before or after use.

Stop Use and ask a doctor if

• condition persists for more than 3 days or worsens
• symptoms clear up and occur again within a few days.

Keep Out Of Reach Of Children

If swallowed, get medical help or contact a Poison Control Center right away.

Directions

Apply a thin layer of the cream to affected area and massage gently as soon as possible after minor bruise. Repeat 3 times a day or as needed. If heat or ice is applied, wait 5 minutes before applying the cream.

Other information

• Store at room temperature (20–25 °C / 68–77 °F).
• Protect from freezing and excessive heat.

Inactive ingredients

Aqua (Water), Niacinamide, Ceramide NP, Aloe Barbadensis Leaf Extract, Propylene Glycol, Tocopherol (Vitamin E), Phytonadione (Vitamin K1), Ascorbic Acid (Vitamin C), Ceramide AP, Phenoxyethanol, Carbomer, Triethanolamine

Questions or comments?

Please contact support@supreh.com